DRUG LABEL: Homeopathic Allergy Formula
NDC: 10578-016 | Form: TABLET
Manufacturer: Indiana Botanic Gardens
Category: homeopathic | Type: HUMAN OTC DRUG LABEL
Date: 20150114

ACTIVE INGREDIENTS: ONION 4 [hp_C]/1 1; APIS MELLIFERA 4 [hp_C]/1 1; ARSENIC TRIOXIDE 4 [hp_C]/1 1; EUPHRASIA STRICTA 4 [hp_C]/1 1; STRYCHNOS NUX-VOMICA SEED 4 [hp_C]/1 1
INACTIVE INGREDIENTS: DEXTROSE; MAGNESIUM STEARATE; SILICON DIOXIDE

Homeopathic Allergy Formula

Suggested Use:

Adults and children over 12 years, take 1 to 2 tablets, dissolve under tongue or chew 3 times a day until symptoms appear to reduce, then once daily to maintain control, or as directed by a health care professional. Can be used prior to allergy season 2 times per day.

STOP USE

If symptoms persist for more than 10 days consult a health professional.

Warning:

If you are taking any medications or are pregnant or breast feeding do not use prior to consulting a physician.

KEEP OUT OF REACH OF CHILDREN.

For your protection, this container has an outer safety seal.

(Do not accept if missing or broken.)

Best if used by date on bottle. Store in a dry cool place.

Any Questions?

1-800-644-8327

website: www.botanicchoice.com

INDICATIONS AND USAGE

For sneezing, runny nose, red and itchy eyes, nose, throat or ears.

PURPOSE

For sneezing, runny nose, red and itchy eyes, nose, throat or ears

Ingredients:

Red onion ...................................4C HPUS

Honeybee ..................................4C HPUS

Arsenic trioxide ..........................4C HPUS

Eyebright ....................................4C HPUS

Poison nut...................................4C HPUS

The letters "HPUS" indicate that the components in this product are officially monographed in the Homeopathic Pharmacopoeia of the United States.

Inactive Ingredients:

Dextrose, Magnesium Stearate, Silica.

DISTRIBUTED BY: INDIANA BOTANIC GARDENS, INC.

3401 W. 37TH AVE. HOBART, IN 46342

Botanic Choice

Natural Remedies Since 1910

NDC 10578-016-90

Homeopathic Allergy Relief

For sneezing, runny nose, red and itchy eyes, nose, throat or ears.

300 mg.

Doctor Recommended for Effectiveness & Potency

90 TABLETS